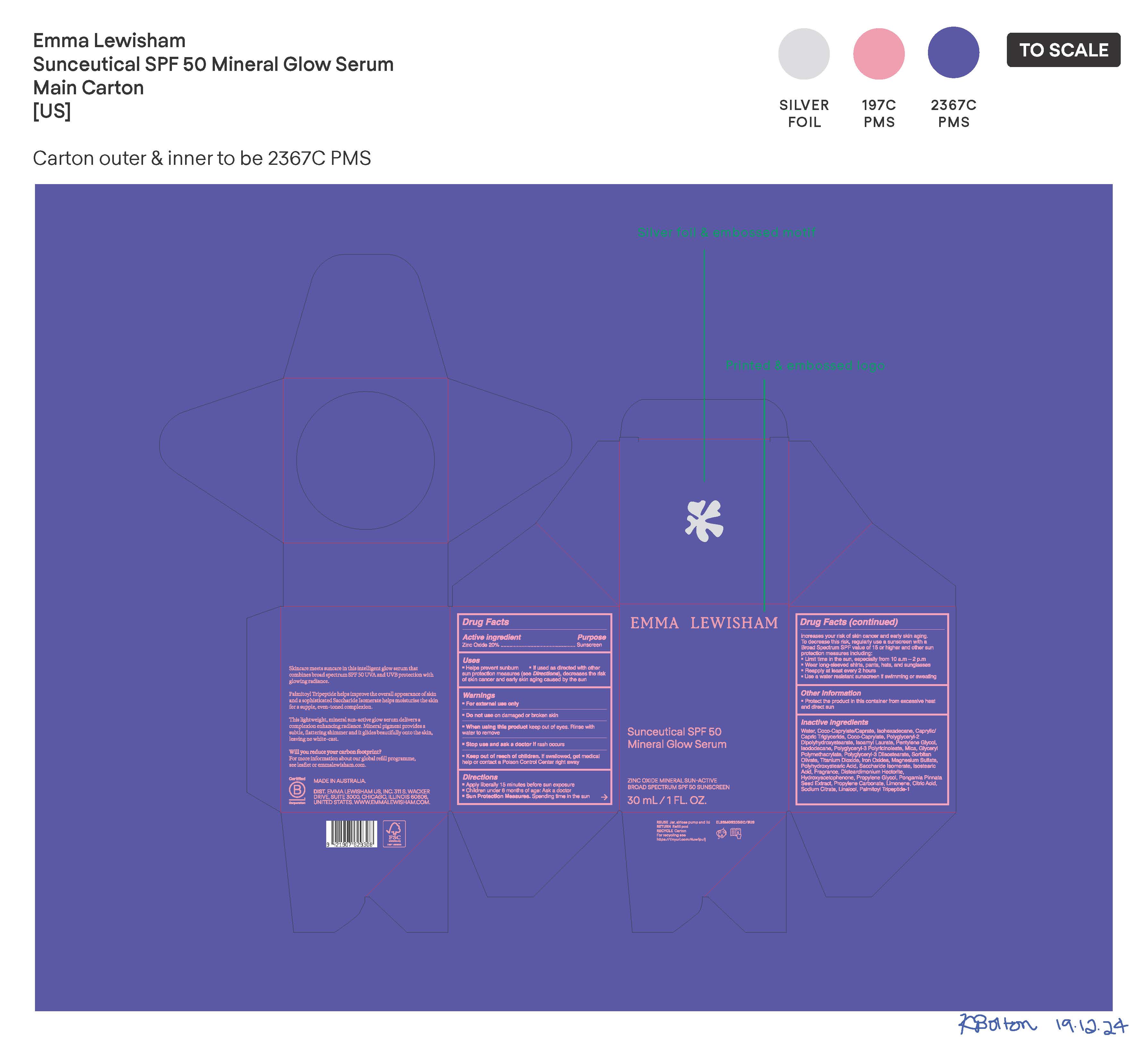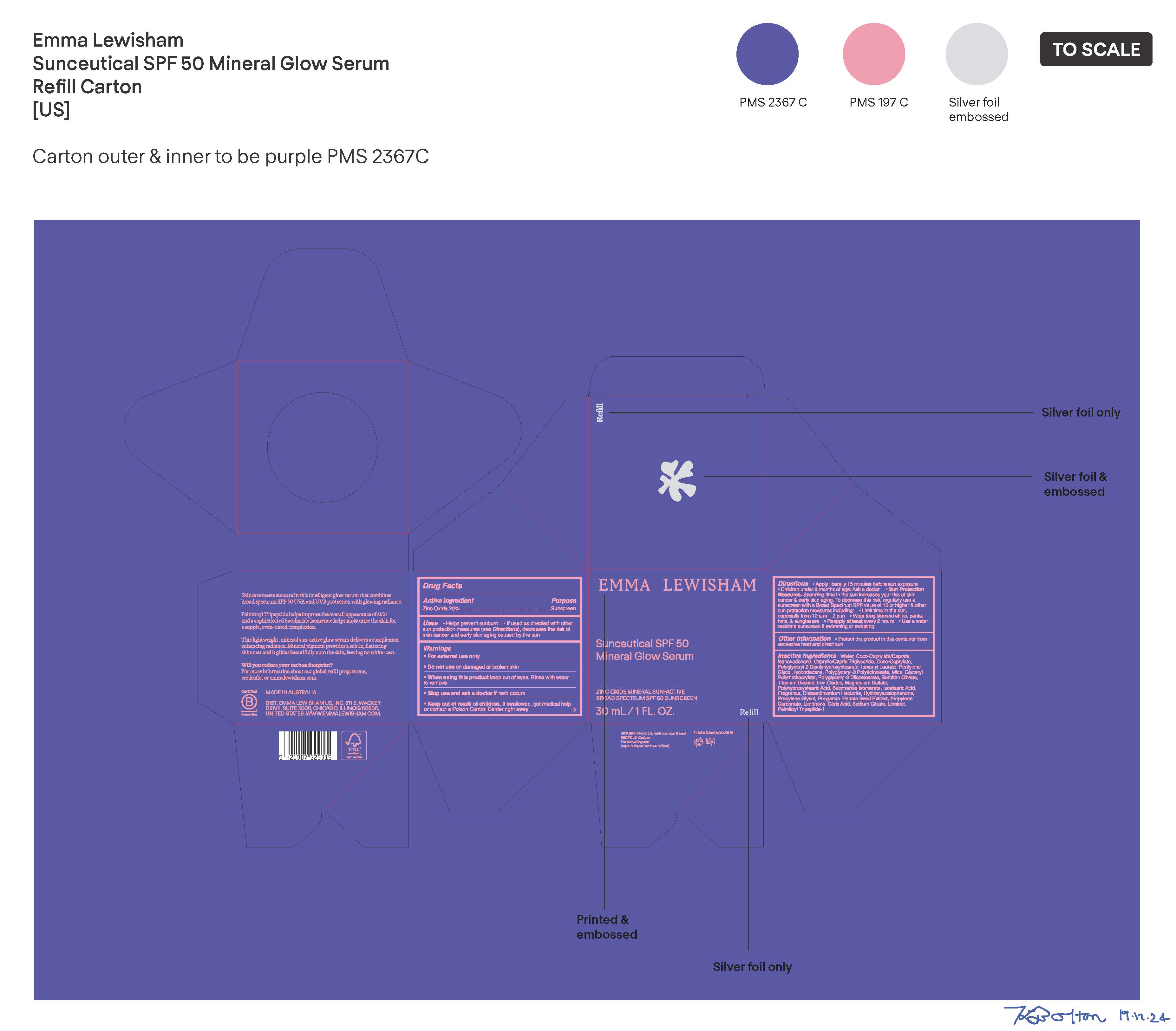 DRUG LABEL: Sunceutical SPF 50 Mineral Glow Serum
NDC: 70157-367 | Form: CREAM
Manufacturer: Baxter Laboratories Pty. Ltd.
Category: otc | Type: HUMAN OTC DRUG LABEL
Date: 20250120

ACTIVE INGREDIENTS: ZINC OXIDE 20 g/100 mL
INACTIVE INGREDIENTS: IRON OXIDES; POLYGLYCERYL-2 DIPOLYHYDROXYSTEARATE; PENTYLENE GLYCOL; WATER; COCO-CAPRYLATE; SORBITAN OLIVATE; ISOSTEARIC ACID; PROPYLENE GLYCOL; CITRIC ACID; SODIUM CITRATE; ISOHEXADECANE; CAPRYLIC/CAPRIC TRIGLYCERIDE; ISOAMYL LAURATE; MICA; POLYGLYCERYL-3 DIISOSTEARATE; LIMONENE, (+/-)-; PALMITOYL TRIPEPTIDE-1; SACCHARIDE ISOMERATE; PROPYLENE CARBONATE; POLYHYDROXYSTEARIC ACID (2300 MW); TITANIUM DIOXIDE; MAGNESIUM SULFATE; DISTEARDIMONIUM HECTORITE; COCO-CAPRYLATE/CAPRATE; ISODODECANE; GLYCERYL POLYMETHACRYLATE (300000 MPA.S); PONGAMIA PINNATA SEED; LINALOOL, (+/-)-; POLYGLYCERYL-3 PENTARICINOLEATE; HYDROXYACETOPHENONE

Sunceutical SPF 50 Mineral Glow Serum

Active ingredient Purpose

Zinc Oxide 20% Suncreen

Uses

- Helps prevent
- If used as directed with other sun protect measures (see Directions), decreases the risk of skin cancer and early skin aging caused by the sun

- Keep out of reach of children. If swallowed, get medical help or contact a Poison Control Center right away.

Stop use and ask a doctor if rash occurs.

Warnings

- For external use only
- Do not use on damaged or broken skin
- When using this product keep out of eyes. Rinse with water to remove.

Directions

- Apply liberally 15 minutes before sun exposure
- Children under 6 months of age: Ask a doctor
- Sun Protection Measures. Spending time in the sun increases your risk of skin cancer and early skin aging. To decrease this risk, regularly use a sunscreen with a Broad Spectrum SPF value of 15 or higher and other sun protection measures including:
- Limit time in the sun, especially from 10 a.m. - 2 p.m.
- Wear long-sleeved shirts, pants, hats, and sunglasses
- Reapply at least every 2 hours
- Use a water resistant sunscreen if swimming or sweating

Other information

- Protect the product in the container from excessive heat and direct

Inactive ingredients

Water, Coco-Caprylate/Caprate, Isohexadecane, Caprylic/Capric Triglyceride, Coco-Caprylate, Polyglyceryl-2 Dipolyhydroxystearate, Isoamyl Laurate, Pentylene Glycol, Isododecane, Polyglyceryl-3 Polyricinoleate, Mica, Glyceryl Polymethacrylate, Polyglyceryl-3 Diisostearate, Sorbitan Olivate, Titantium Dioxide Iron Oxides, Magnesium Sulfate, Polyhydroxystearic Acid, Saccharide Isomerate, Isostearic Acid, Fragrance, Disteardimonium Hectorite, Hydroxyacetophenone, Propylene Glycol, Pongamia Pinnata Seed Extract, Propylene Carbonate, Limonene, Citric Acid, Sodium Citrate, Linalool, Palmitoyl Tripeptide-1

PACKAGE LABEL

Emma Lewisham

Sunceutical SPF 50 Mineral Glow Serum

Zinc Oxide Mineral Sun-Active

Broad Spectrum SPF 50 Sunscreen

30mL/ 1 FL. OZ.